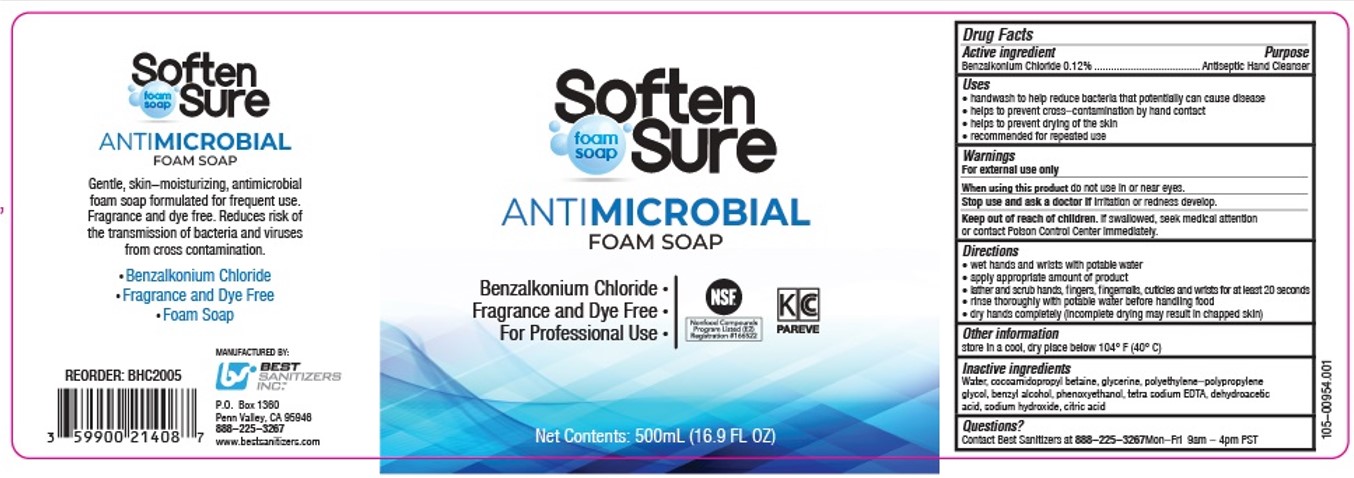 DRUG LABEL: SoftenSure Antimicrobial Foam
NDC: 59900-216 | Form: LIQUID
Manufacturer: Best Sanitizers, Inc
Category: otc | Type: HUMAN OTC DRUG LABEL
Date: 20241213

ACTIVE INGREDIENTS: BENZALKONIUM CHLORIDE 0.13 mg/100 mL
INACTIVE INGREDIENTS: COCAMIDOPROPYL BETAINE; WATER; TETRASODIUM EDTA; CITRIC ACID MONOHYDRATE; PHENOXYETHANOL; BENZYL ALCOHOL; POLOXAMER 124; SODIUM HYDROXIDE; DEHYDROACETIC ACID; GLYCERIN

SoftenSure Antimicrobial Foam Soap 59900-216

Active ingredient

Benzalkonium Chloride 0.12%

Purpose

Antiseptic Hand Cleanser

Uses

• handwash to help reduce bacteria that potentially can cause disease

• helps to prevent cross-contamination by hand contact

• helps to prevent drying of the skin

• recommended for repeated use

Warnings

For external use only

When using this product do not use in or near eyes.

Stop use and ask a doctor if irritation or redness develop.

Keep out of reach of children. If swallowed, seek medical attention or contact Poison Control Center immediately.

Directions

• wet hands and wrists with potable water

• apply appropriate amount of product

• lather and scrub hands, fingers, fingernails, cuticles, and wrists for at least 20 seconds

• rinse thoroughly with potable water before handling food

• dry hands completely (incomplete drying may result in chapped skin)

Other information

store in a cool, dry place below 104° F (40° C)

Inactive ingredients

Water, cocamidopropyl betaine, glycerine, polyethylene-polypropylene glycol, benzyl alcohol, phenoxyethanol, tetrasodium EDTA, dehydroacetic acid, sodium hydroxide, citric acid

Questions?

Contact Best Sanitizers at 888-225-3267 Mon-Fri 9am-4 pm PST

PACKAGE LABEL

foam

soap

Soften

Sure

ANTIMICROBIAL

FOAM SOAP

Benzalkonium Chloride •

Fragrance and Dye Free •

For Professional Use •

NSF

Nonfood Compounds

Program Listed (E2)

Registration #166522

KC

PAREVE

Net Contents: 500mL (16.9 FL OZ)